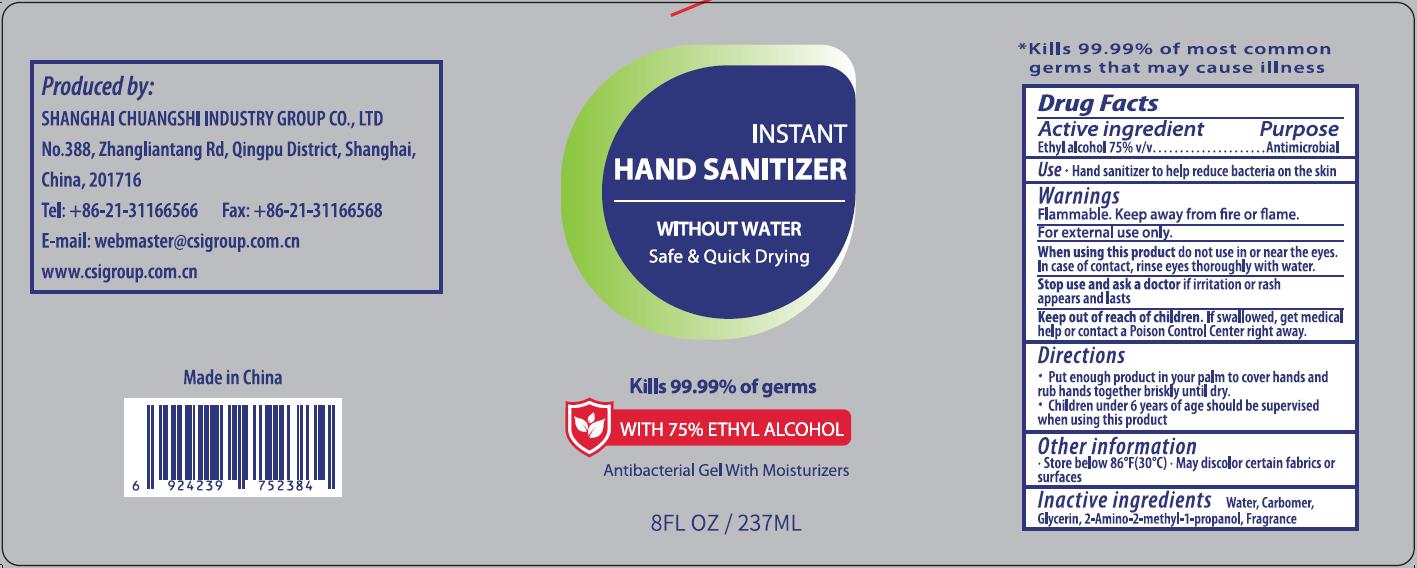 DRUG LABEL: INSTANT HAND SANITIZER
NDC: 73557-261 | Form: GEL
Manufacturer: Shanghai Chuangshi Industry Group Co., Ltd
Category: otc | Type: HUMAN OTC DRUG LABEL
Date: 20200611

ACTIVE INGREDIENTS: ALCOHOL 177.75 mL/237 mL
INACTIVE INGREDIENTS: GLYCERIN; WATER; CARBOMER HOMOPOLYMER, UNSPECIFIED TYPE; LEMON OIL; AMINOMETHYLPROPANOL

CSI, Hand Sanitizer, Gel, Alcohol 75%; 237mL

Active Ingredient(s)

Ethyl alcohol 75% v/v. Purpose: Antimicrobial

Purpose

Antibacterial

Use

Hand sanitizer to help reduce bacteria on the skin.

Warnings

Flammable. Keep away from fire or flame.

Do not use

For external use only.

When using this product do not use in or near the eyes.

If case of contact, rinse eyes thoroughly with water.

Stop use and ask a doctor if irritation or rash appears and lasts.

Keep out of reach of children. If swallowed, get medical help or contact a Poison Control Center right away.

Directions

- Put enough product in your palm to cover hands and rub hands together briskly until dry.
- Children under 6 years of age should be supervised when using this product.

Other information

- Store below 86℉(30℃).
- May discolor certain fabrics or surfaces.

Inactive ingredients

Water, Carbomer, Glycerin, 2-Amino-2-methyl-1-propanol, Fragrance.